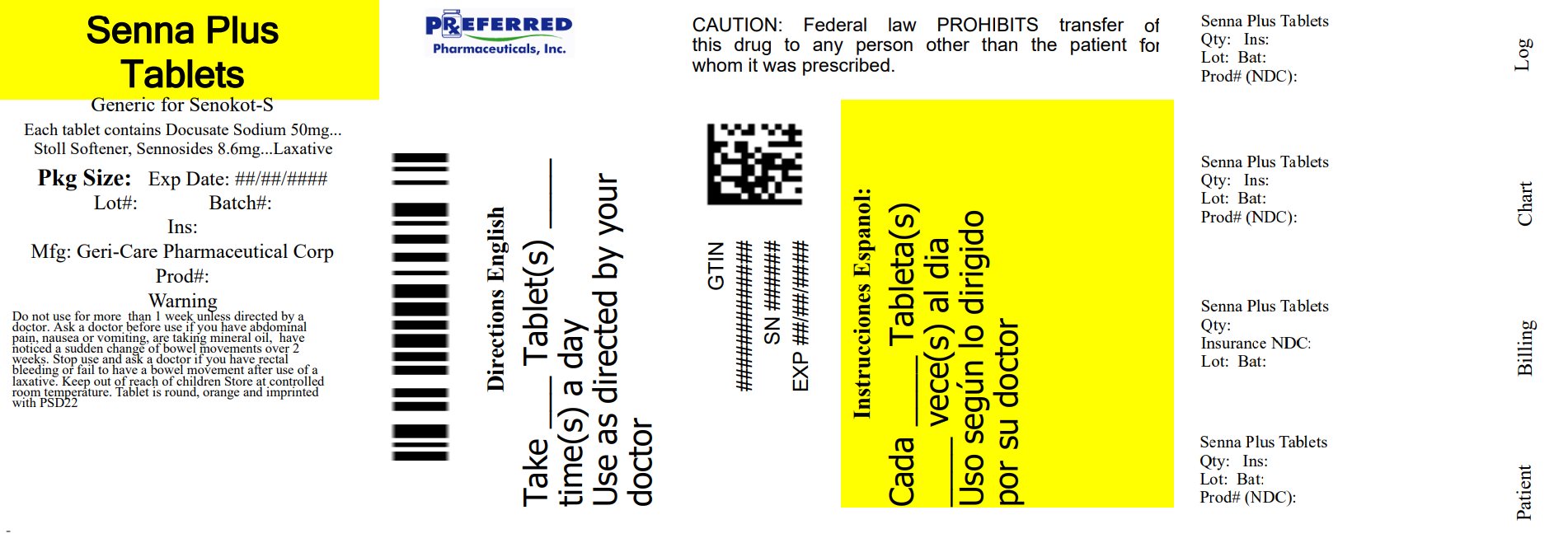 DRUG LABEL: SENNA-PLUS
NDC: 68788-8780 | Form: TABLET
Manufacturer: Preferred Pharmaceuticals Inc.
Category: otc | Type: HUMAN OTC DRUG LABEL
Date: 20260122

ACTIVE INGREDIENTS: SENNOSIDES 8.6 mg/1 1; DOCUSATE SODIUM 50 mg/1 1
INACTIVE INGREDIENTS: MICROCRYSTALLINE CELLULOSE; CROSCARMELLOSE SODIUM; ANHYDROUS DIBASIC CALCIUM PHOSPHATE; MAGNESIUM STEARATE; POLYETHYLENE GLYCOL, UNSPECIFIED; HYPROMELLOSE, UNSPECIFIED; FD&C YELLOW NO. 6; TITANIUM DIOXIDE; TALC; SILICON DIOXIDE

hst 455b (555)

Active ingredient (in each tablet)

Docusate Sodium 50 mg
Sennosides 8.6 mg

Purpose

Stool softener

Laxative

Uses

- relieves occasional constipation (irregularity)
- this product generally produces a bowel movement in 6 to 12 hours

Warnings

Do not use for more than one week unless directed by a doctor

Ask a doctor before use if you

- have abdominal pain, nausea or vomiting
- are taking mineral oil
- have noticed a sudden change in bowel habits that lasts over two weeks

Stop use and ask a doctor if you have rectal bleeding or fail to have a bowel movement after use of a laxative.
These may indicate a serious condition.

If pregnant or breast-feeding, ask a health professional before use.

Keep out of reach of children. In case of overdose, get medical help or contact a Poison Control Center right away.

Directions

• do not exceed 8 tablets in 24 hours

Age | Starting Dose | Maximum Dose
adults and children 12 years of age and older | 2 tablets once a day preferably at bedtime; increase as needed, or as directed by a doctor | 4 tablets in the morning and 4 tablets at bedtime
children under 12 years | ask a doctor

Other information

- each tablet contains: calcium 20 mg, sodium 3 mg
- store at controlled room temperature
  Tamper Evident: Do not use if imprinted seal under cap is missing or broken.
- product of India

Repackaged By: Preferred Pharmaceuticals Inc.

Inactive ingredients

cellulose, croscarmellose sodium, dicalcium phosphate, FD&C yellow #6 lake, hypromellose, magnesium stearate, PEG, silica, talc, titanium dioxide.